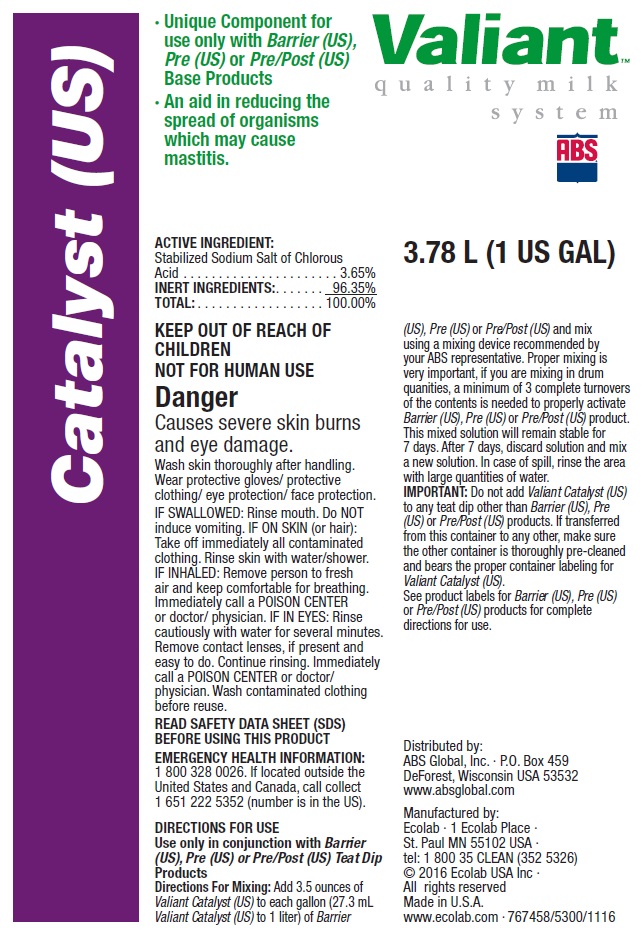 DRUG LABEL: ABS Valiant Catalyst (US)
NDC: 59282-105 | Form: SOLUTION
Manufacturer: ABS Global Inc.
Category: animal | Type: OTC ANIMAL DRUG LABEL
Date: 20190709

ACTIVE INGREDIENTS: SODIUM CHLORITE 36.5 mg/1 mL
INACTIVE INGREDIENTS: WATER

KEEP OUT OF REACH OF CHILDREN

NOT FOR HUMAN USE

Danger

Causes severe skin burns and eye damage.

Wash skin thoroughly after handling. Wear protective gloves/ protective clothing/ eye protection/ face protection.

VETERINARY INDICATIONS

DIRECTIONS FOR USE

Use only in conjunction with Barrier (US), Pre (US) or Pre/Post (US) Teat Dip Products

Directions For Mixing: Add 3.5 ounces of Valiant Catalyst (US) to each gallon (27.3 mL Valiant Catalyst (US) to 1 liter) of Barrier (US), Pre (US) or Pre/Post (US) and mix using a mixing device recommended by your ABS representative. Proper mixing is very important, if you are mixing in drum quanities, a minimum of 3 complete turnovers of the contents is needed to properly activate Barrier (US), Pre (US) or Pre/Post (US) product. This mixed solution will remain stable for 7 days. After 7 days, discard solution and mix a new solution. In case of spill, rinse the area with large quantities of water.

IMPORTANT: Do not add Valiant Catalyst (US) to any teat dip other than Barrier (US), Pre (US) or Pre/Post (US) products. If transferred from this container to any other, make sure the other container is thoroughly pre-cleaned and bears the proper container labeling for Valiant Catalyst (US). See product labels for Barrier (US), Pre (US) or Pre/Post (US) products for complete directions for use.

OTHER SAFETY INFORMATION

IF SWALLOWED: Rinse mouth. Do NOT induce vomiting. IF ON SKIN (or hair): Take off immediately all contaminated clothing. Rinse skin with water/shower. IF INHALED: Remove person to fresh air and keep comfortable for breathing. Immediately call a POISON CENTER or doctor/ physician. IF IN EYES: Rinse cautiously with water for several minutes. Remove contact lenses, if present and easy to do. Continue rinsing. Immediately call a POISON CENTER or doctor/ physician. Wash contaminated clothing before reuse.

READ SAFETY DATA SHEET (SDS) BEFORE USING THIS PRODUCT

EMERGENCY HEALTH INFORMATION: 1 800 328 0026. If located outside the United States and Canada, call collect 1 651 222 5352 (number is in the US).

PACKAGE LABEL

Valiant

quality milk system

Catalyst (US)

Unique Component for use only with Barrier (US), Pre (US) or Pre/Post (US) Base Products

An aid in reducing the spread of organisms which may cause mastitis.

ACTIVE INGREDIENT:

Stabilized Sodium Salt of Chlorous Acid ...................... 3.65%

INERT INGREDIENTS: ....... 96.35%

TOTAL: .................. 100.00%

3.78 L (1 US GAL)

Distributed by:

ABS Global, Inc. · P.O. Box 459 DeForest, Wisconsin USA 53532

www.absglobal.com

Manufactured by:

Ecolab · 1 Ecolab Place ·

St. Paul MN 55102 USA ·

tel: 1 800 35 CLEAN (352 5326)

© 2016 Ecolab USA Inc ·

All rights reserved

Made in U.S.A.

www.ecolab.com · 767458/5300/1116